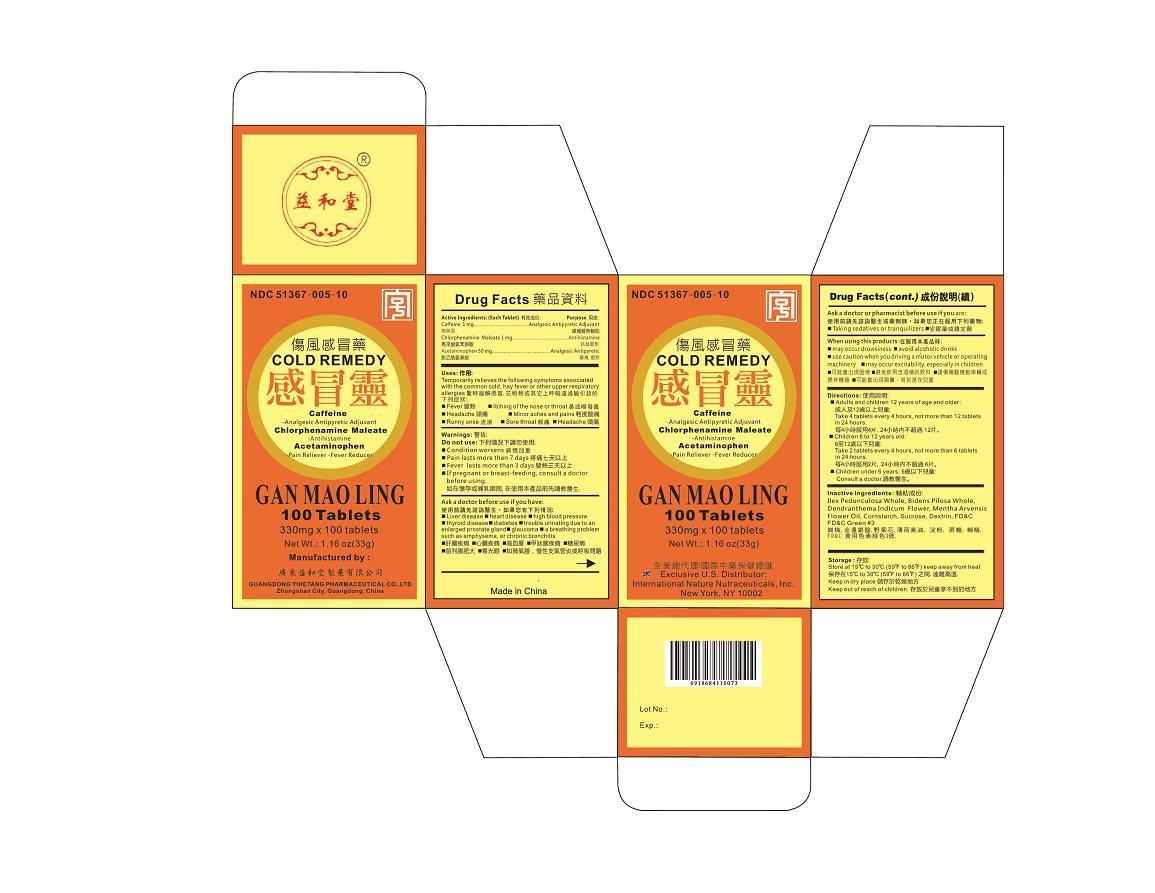 DRUG LABEL: Cold Remedy Gan Mao Ling
NDC: 51367-005 | Form: TABLET
Manufacturer: International Nature Nutraceuticals
Category: otc | Type: HUMAN OTC DRUG LABEL
Date: 20130315

ACTIVE INGREDIENTS: CAFFEINE 1 mg/1 1; CHLORPHENIRAMINE MALEATE 1 mg/1 1; ACETAMINOPHEN 50 mg/1 1
INACTIVE INGREDIENTS: BIDENS PILOSA WHOLE; DENDRANTHEMA INDICUM FLOWER; MENTHA ARVENSIS FLOWER OIL; ILEX PEDUNCULOSA WHOLE

Drug Facts

Active Ingredients

Caffeine- 1mg

Chlorpheniramine Maleate- 1mg

Acetaminophen- 50mg

When using this product

May occur drowsiness

avoid alcoholic drinks

use caution when you driving a motor vehicle or operating machinery

may occur excitability especially in children

Uses

Temporarily relieves the following symptoms associated with the common cold, hay fever, or other upper respiratory allergies

- fever
- headache
- runny nose
- itching of the nose or throat
- minor aches and pains
- sore throat

Warnings

Do not use if:

- Condition worsens
- pain lasts more than 7 days
- fever lasts more than 3 days
- if pregnant or breast-feeding, consult a doctor before using

Ask a doctor/pharmacist before use

Ask before use if you have:

- liver disease
- heart disease
- high blood pressure
- thyroid disease
- diabetes
- trouble urinating due to an enlarged prostate gland
- glaucoma
- a breathing problem such as emphysema or chronic bronchitis
- taking sedatives or tranquilizers

Directions:

Adults and children 12 years of age and older:

- take 4 tablets every 4 hours, not more than 12 tablets in 24 hours

Children 6 to 12 years old

- take 2 tablets every 4 hours, not more than 6 tablets in 24 hours

Children under 6 years:

- consult a doctor

Inactive Ingredients

金盏银盘 Bidens Pilosa Whole 野菊花。 Dendranthema indicum flower. 薄荷油. Mentha arvensis flower oil. 岗梅 ilex Pedunculosa whole

Storage

Store at 15°C to 30°C (59°F to 86°F)

keep away from heat

keep in dry place